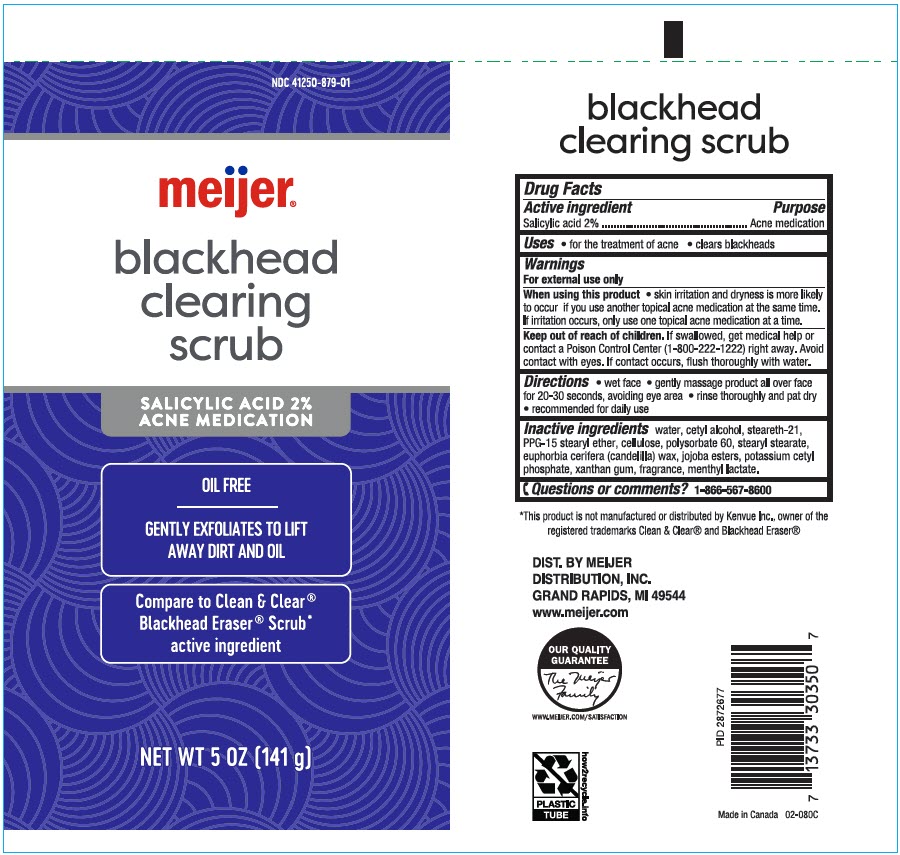 DRUG LABEL: Meijer Blackhead Clearing Scrub
NDC: 41250-879 | Form: CREAM
Manufacturer: Meijer Distribution, Inc
Category: otc | Type: HUMAN OTC DRUG LABEL
Date: 20231108

ACTIVE INGREDIENTS: Salicylic Acid 20 mg/1 g
INACTIVE INGREDIENTS: Water; Cetyl Alcohol; Steareth-21; POLYPROPYLENE GLYCOL 15 STEARYL ETHER; POWDERED CELLULOSE; Polysorbate 60; Stearyl Stearate; CANDELILLA WAX; HYDROLYZED JOJOBA ESTERS (ACID FORM); Potassium Cetyl Phosphate; Xanthan Gum; METHYL LACTATE, (-)-

Meijer® Blackhead Clearing Scrub
Acne medication

Drug Facts

Active ingredient

Salicylic Acid 2.0%

Purpose

Acne medication

Uses

- for the treatment of acne
- clears blackheads

Warnings

For external use only

When using this product

- skin irritation and dryness is more likely to occur if you use another topical acne medication at the same time. If this occurs, use only one topical acne medication at a time.

Keep out of reach of children. If swallowed, get medical help or contact a Poison Control Center right away. Avoid contact with eyes. If contact occurs, flush thoroughly with water.

Directions

- wet face
- gently massage product all over face for 20-30 seconds, avoiding eye area
- rinse thoroughly and pat dry
- recommended for daily use

Inactive ingredients

Water, Cetyl Alcohol, Steareth-21, PPG-15 Stearyl Ether, Cellulose, Polysorbate 60, Stearyl Stearate, Euphorbia Cerifera (Candelilla) Wax, Jojoba Esters, Potassium Cetyl Phosphate, Xanthan Gum, Fragrance, Methyl Lactate.

Questions or comments?

1-866-567-8600

DIST. BY MEIJER
DISTRIBUTION, INC.
GRAND RAPIDS, MI 49544

PRINCIPAL DISPLAY PANEL - 141 g Tube Label

NDC 41250-879-01

meijer®

blackhead
clearing
scrub

SALICYLIC ACID 2%
ACNE MEDICATION

OIL FREE

GENTLY EXFOLIATES TO LIFT
AWAY DIRT AND OIL

Compare to Clean & Clear®
Blackhead Eraser® Scrub*
active ingredient

NET WT 5 OZ (141 g)